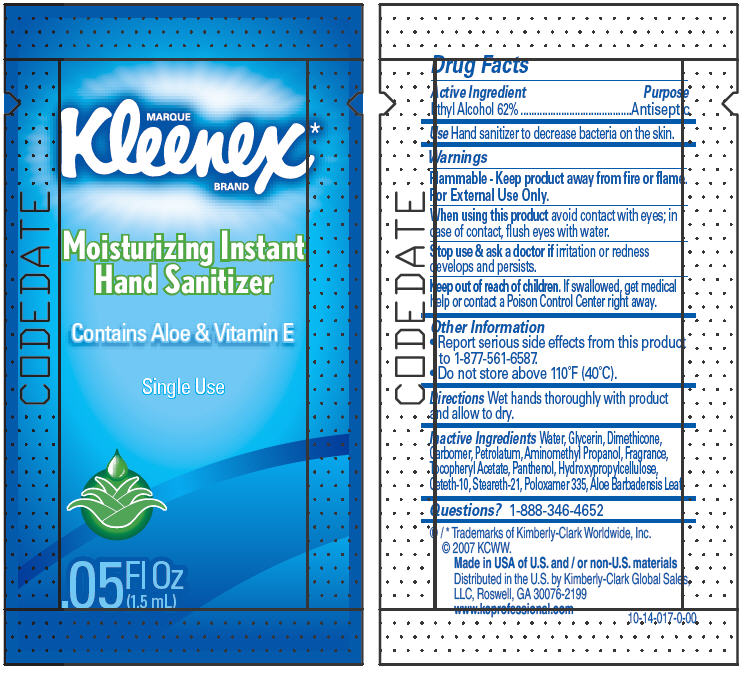 DRUG LABEL: Kleenex Moisturizing Instant Hand Sanitizer
NDC: 55118-480 | Form: SOLUTION
Manufacturer: Kimberly-Clark Corporation
Category: otc | Type: HUMAN OTC DRUG LABEL
Date: 20140924

ACTIVE INGREDIENTS: Alcohol 62 mL/100 mL
INACTIVE INGREDIENTS: Water; Glycerin; Dimethicone; Petrolatum; Aminomethylpropanol; Panthenol; Hydroxypropyl Cellulose (Type H); Ceteth-10; Steareth-21; Poloxamer 335; Aloe Vera Leaf

MARQUE
kleenex®
BRAND
MOISTURIZING INSTANT HAND SANITIZER

Drug Facts

Active Ingredient

Ethyl Alcohol 62%

Purpose

Antiseptic

Use

Hand sanitizer to decrease bacteria on the skin.

Warnings

Flammable - Keep product away from fire or flame.

For External Use Only.

When using this product avoid contact with eyes; in case of contact, flush eyes with water.

Stop use & ask a doctor if irritation or redness develops and persists.

Keep out of reach of children. If swallowed, get medical help or contact a Poison Control Center right away.

Directions

Wet hands thoroughly with product and allow to dry.

Other Information

- Report serious side effects from this product to 1-877-561-6587.
- Do not store above 110°F (40°C).

Inactive Ingredients

Water, Glycerin, Dimethicone, Carbomer, Petrolatum, Aminomethyl Propanol, Fragrance, Tocopheryl Acetate, Panthenol, Hydroxypropylcellulose, Ceteth-10, Steareth-21, Poloxamer 335, Aloe Barbadensis Leaf

Questions?

1-888-346-4652

Distributed in the U.S. by Kimberly-Clark Global Sales, LLC, Roswell, GA 30076-2199

www.kcprofessional.com

PRINCIPAL DISPLAY PANEL - 1.5 mL Pouch Label

MARQUE
Kleenex*
BRAND

Moisturizing Instant
Hand Sanitizer

Contains Aloe & Vitamin E

Single Use

.05
Fl Oz
(1.5 mL)